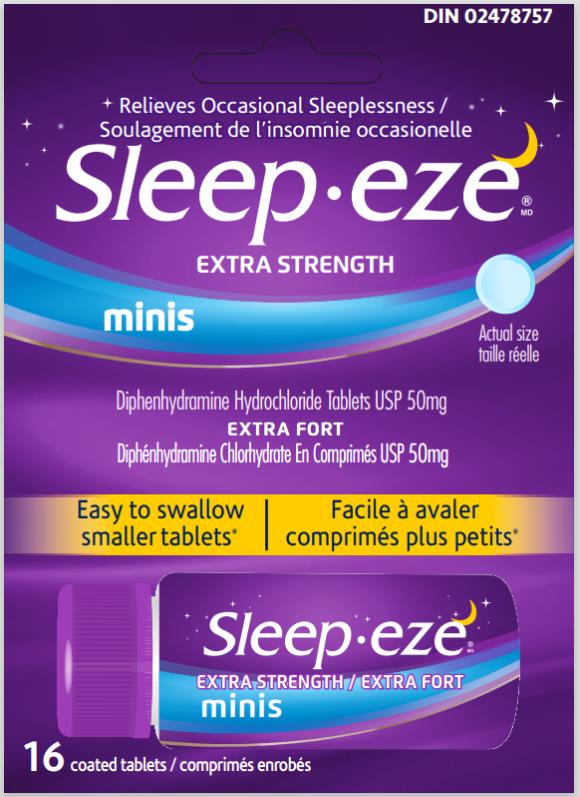 DRUG LABEL: SleepEze minis
NDC: 63029-926 | Form: TABLET
Manufacturer: Medtech Products Inc.
Category: otc | Type: HUMAN OTC DRUG LABEL
Date: 20240118

ACTIVE INGREDIENTS: DIPHENHYDRAMINE HYDROCHLORIDE 50 mg/1 1
INACTIVE INGREDIENTS: CROSCARMELLOSE SODIUM; DIBASIC CALCIUM PHOSPHATE DIHYDRATE; FD&C BLUE NO. 1 ALUMINUM LAKE; HYPROMELLOSES; LACTOSE MONOHYDRATE; MAGNESIUM STEARATE; MICROCRYSTALLINE CELLULOSE; MINERAL OIL; SILICON DIOXIDE; STEARIC ACID; TALC; TITANIUM DIOXIDE; TRIACETIN

SleepEze 50 mg Minis_Export only 63029-926-16

Drug Facts

Purpose

Diphenhydramine Hydrochloride 50 mg…………………………....Nighttime sleep aid

Warnings

Do not use

●if you are elderly, as this drug may cause excitation rather than sedation ●with any other product containing diphenhydramine, even one used on skin ●in children under 12 years of age

Ask a doctor or pharmacist before use if you

●have ▪a breathing problem such as emphysema or chronic bronchitis ▪glaucoma ▪difficulty urinating ●take sedatives or tranquilizers ●are pregnant or breastfeeding

When using this product

avoid drinking alcohol

Stop use and ask a doctor if

sleeplessness continues for more than 2 weeks. Sleeplessness may be a symptom of a serious underlying medical illness

Keep out of reach of children.

In case of overdose, call a poison control centre or get medical help right away.

Directions

Adults and children 12 years and over: ▪take 1 tablet at bedtime if needed, or as directed by a doctor ▪if you feel drowsy in the morning, consult a doctor or pharmacist as you may require a lower dosage (25 mg) ▪do not take more than directed

Other information

▪ Store at 20° to 25°C

Inactive ingredients

croscarmellose sodium, dibasic calcium phosphate dihydrate, FD&C blue no. 1 aluminum lake, hypromellose, lactose monohydrate, magnesium stearate, microcrystalline cellulose, mineral oil, silica, stearic acid, talc, titanium dioxide, triacetin

Questions?

1-800-443-4908

PRINCIPAL DISPLAY PANEL

Sleep•eze® MD

extra strength minis

DIPHENHYDRAMINE HYDROCHLORIDE TABLETS USP 50 mg

extra fort

DIPHÉNHYDRAMINE CHLORHYDRATE EN COMPRIMÉ USP 50 mg

nighttime sleep aid / la solution contre insomnie

16 coated tablets/ comprimes enrobes

DIN 02478757